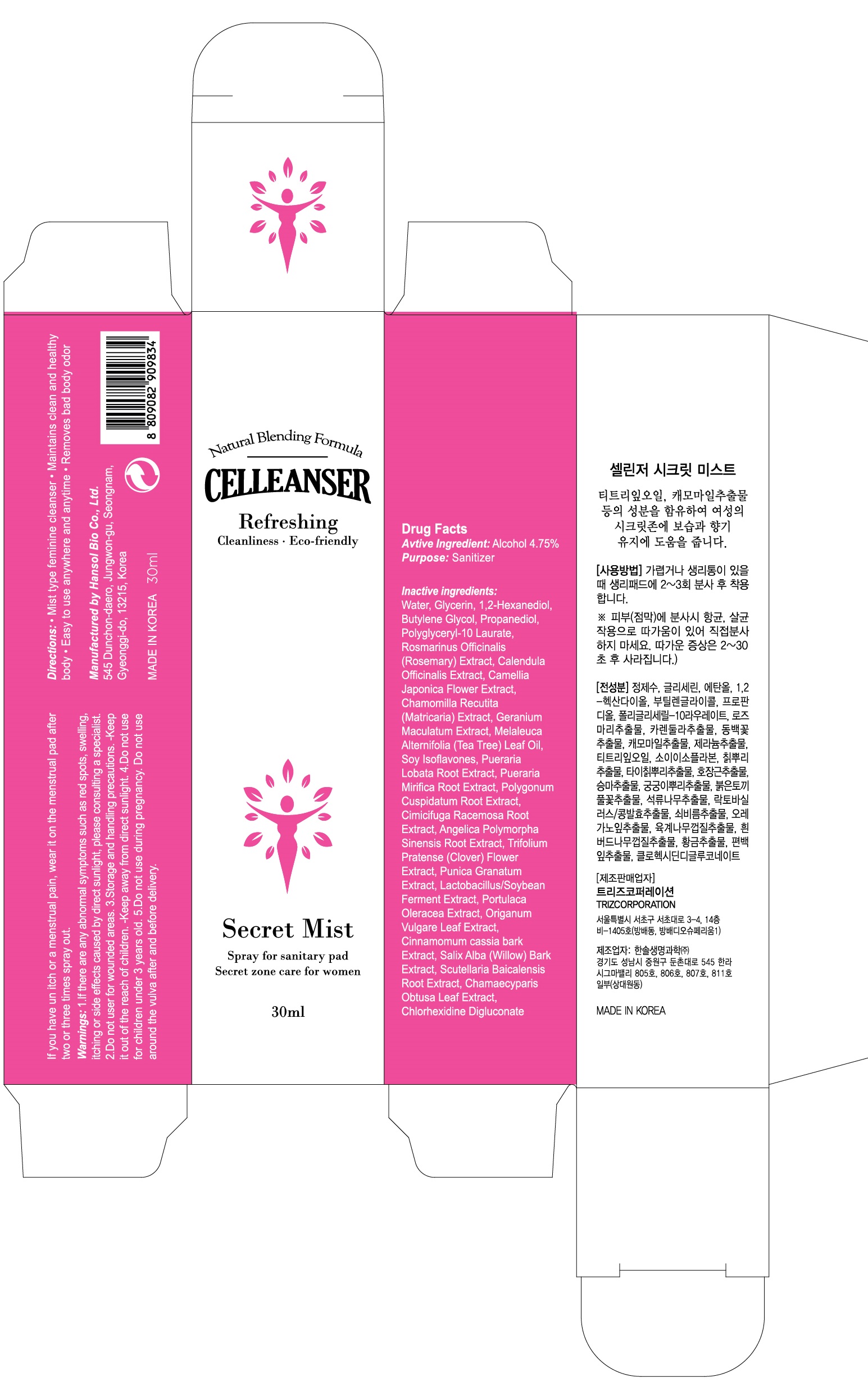 DRUG LABEL: CELLEANSER Secret Mist
NDC: 71910-010 | Form: SPRAY
Manufacturer: Hansol Bio Co.,Ltd
Category: otc | Type: HUMAN OTC DRUG LABEL
Date: 20171206

ACTIVE INGREDIENTS: Alcohol 1.42 g/30 mL
INACTIVE INGREDIENTS: Water; Glycerin

ACTIVE INGREDIENT

Active Ingredient: Alcohol 4.75%

INACTIVE INGREDIENT

Inactive ingredients: Water, Glycerin, 1,2-Hexanediol, Butylene Glycol, Propanediol, Polyglyceryl-10 Laurate, Rosmarinus Officinalis (Rosemary) Extract, Calendula Officinalis Extract, Camellia Japonica Flower Extract, Chamomilla Recutita (Matricaria) Extract, Geranium Maculatum Extract, Melaleuca Alternifolia (Tea Tree) Leaf Oil, Soy Isoflavones, Pueraria Lobata Root Extract, Pueraria Mirifica Root Extract, Polygonum Cuspidatum Root Extract, Cimicifuga Racemosa Root Extract, Angelica Polymorpha Sinensis Root Extract, Trifolium Pratense (Clover) Flower Extract, Punica Granatum Extract, Lactobacillus/Soybean Ferment Extract, Portulaca Oleracea Extract, Origanum Vulgare Leaf Extract, Cinnamomum cassia bark Extract, Salix Alba (Willow) Bark Extract, Scutellaria Baicalensis Root Extract, Chamaecyparis Obtusa Leaf Extract, Chlorhexidine Digluconate

PURPOSE

Purpose: Sanitizer

WARNINGS

Warnings: 1. If there are any abnormal symptoms such as red spots, swelling, itching or side effects caused by direct sunlight, please consulting a specialist. 2. Do not user for wounded areas. 3. Storage and handling precautions. -Keep it out of the reach of children. -Keep away from direct sunlight. 4. Do not use for children under 3 years old. 5. Do not use during pregnancy. Do not use around the vulva after and before delivery.

KEEP OUT OF REACH OF CHILDREN

Keep it out of the reach of children.

Uses

Mist type feminine cleanser. Maintains clean and healthy body. Easy to use anywhere and anytime. Removes bad body odor.

Directions

If you have un itch or a menstrual pain, wear it on the menstrual pad after two or three times spray out.